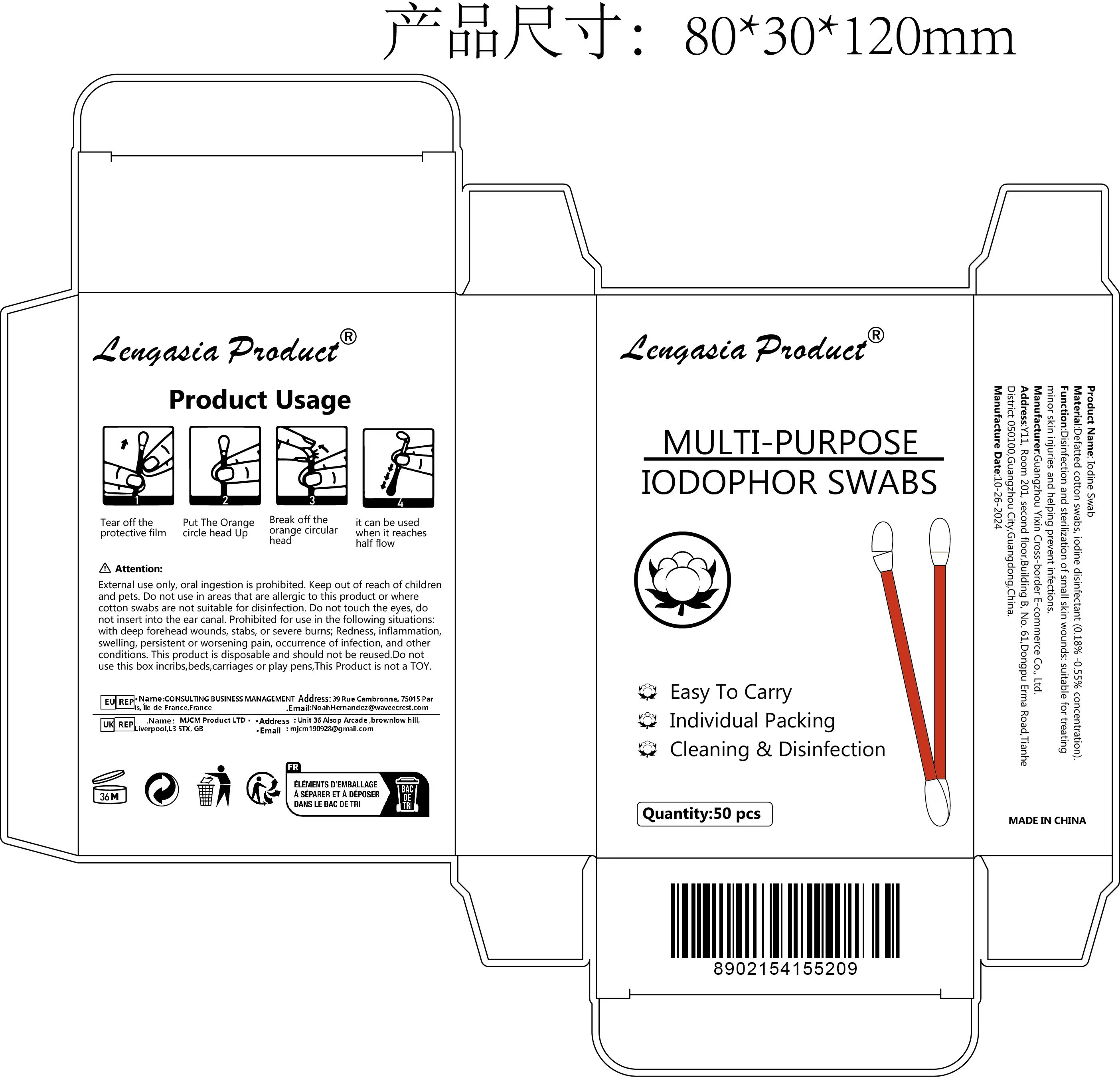 DRUG LABEL: YS Iodine cotton swab
NDC: 84778-015 | Form: SWAB
Manufacturer: Guangzhou Yixin Cross-border E-commerce Co., Ltd.
Category: otc | Type: HUMAN OTC DRUG LABEL
Date: 20241024

ACTIVE INGREDIENTS: IODINE 0.5 g/0.5 g

COMPONENTS

iodine 0.5g

PURPOSE

Disinfection and sterilization of small skin wounds: suitable for treating minor skin injuries and helping prevent infections

INDICATIONS AND USAGE

Tear off the protective filmPut The Orange circle head UpBreak off the orange circular headit can be used when it reaches half flow

WARNINGS

External use only, oral ingestion is prohibited.

Keep out of reach of children and pets.

Do not use in areas that are allergic to this product or where cotton swabs are not suitable for disinfection.

Do not touch the eyes, do not insert into the ear canal.

DOSAGE AND ADMINISTRATION

For external use only.

DO NOT USE

Prohibited for use in the following situations: with deep forehead wounds, stabs, or severe burns;

Redness, inflammation, swelling, persistent or worsening pain, occurrence of infection, and other conditions.

This product is disposable and should not be reused.

Do not use this box incribs,beds,carriages or play pens,This Product is not a TOY.

Do not use in areas that are allergic to this product or where cotton swabs are not suitable for disinfection.

Do not use in the following cases: Deep wounds, puncture wounds or severe burns on the forehead; Redness, inflammation, swelling, persistent or worsening pain, infection, etc.

Keep out of reach of children and pets.

Do not use this box incribs,beds,carriages or play pens,This Product is not a TOY.

INACTIVE INGREDIENT

Defatted cotton swabs